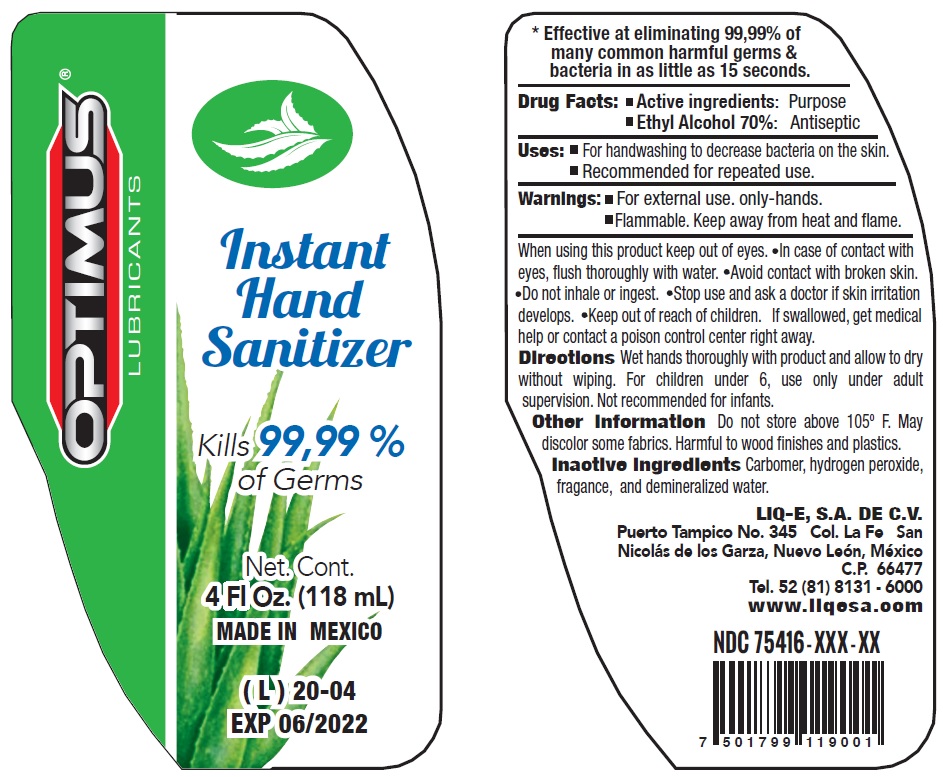 DRUG LABEL: Optimus Instant Hand Sanitizer
NDC: 75416-005 | Form: GEL
Manufacturer: Liq-E, S.A. de C.V.
Category: otc | Type: HUMAN OTC DRUG LABEL
Date: 20200610

ACTIVE INGREDIENTS: ALCOHOL 0.7 mL/1 mL
INACTIVE INGREDIENTS: CARBOMER HOMOPOLYMER, UNSPECIFIED TYPE; HYDROGEN PEROXIDE; WATER

Optimus Instant Hand Sanitizer

Active Ingredients:

Ethyl Alcohol 70%:

Purpose

Antiseptic

Use[S]

- For handwashing to decrease bacteria on the skin.
- Recommended for repeated use.

Warnings

- For external use. only-hands.
- Flammable. Keep away from heat and flame.

When using this product

keep out of eyes.

- In case of contact with eyes, flush thoroughly with water.
- Avoid contact with broken skin.
- Do not inhale or ingest.

Stop use and ask a doctor

if skin irritation develops.

Keep out of reach of children.

If swallowed, get medical help or contact a poison control center right away.

Directions

- Wet hands thoroughly with product and allow to dry without wiping. For children under 6, use only under adult supervision. Not recommended for infants.

Other information

Do not store above 105º F. May discolor some fabrics. Harmful to wood finishes and plastics.

Inactive Ingredients

Carbomer, hydrogen peroxide, fragance, and demineralized water.